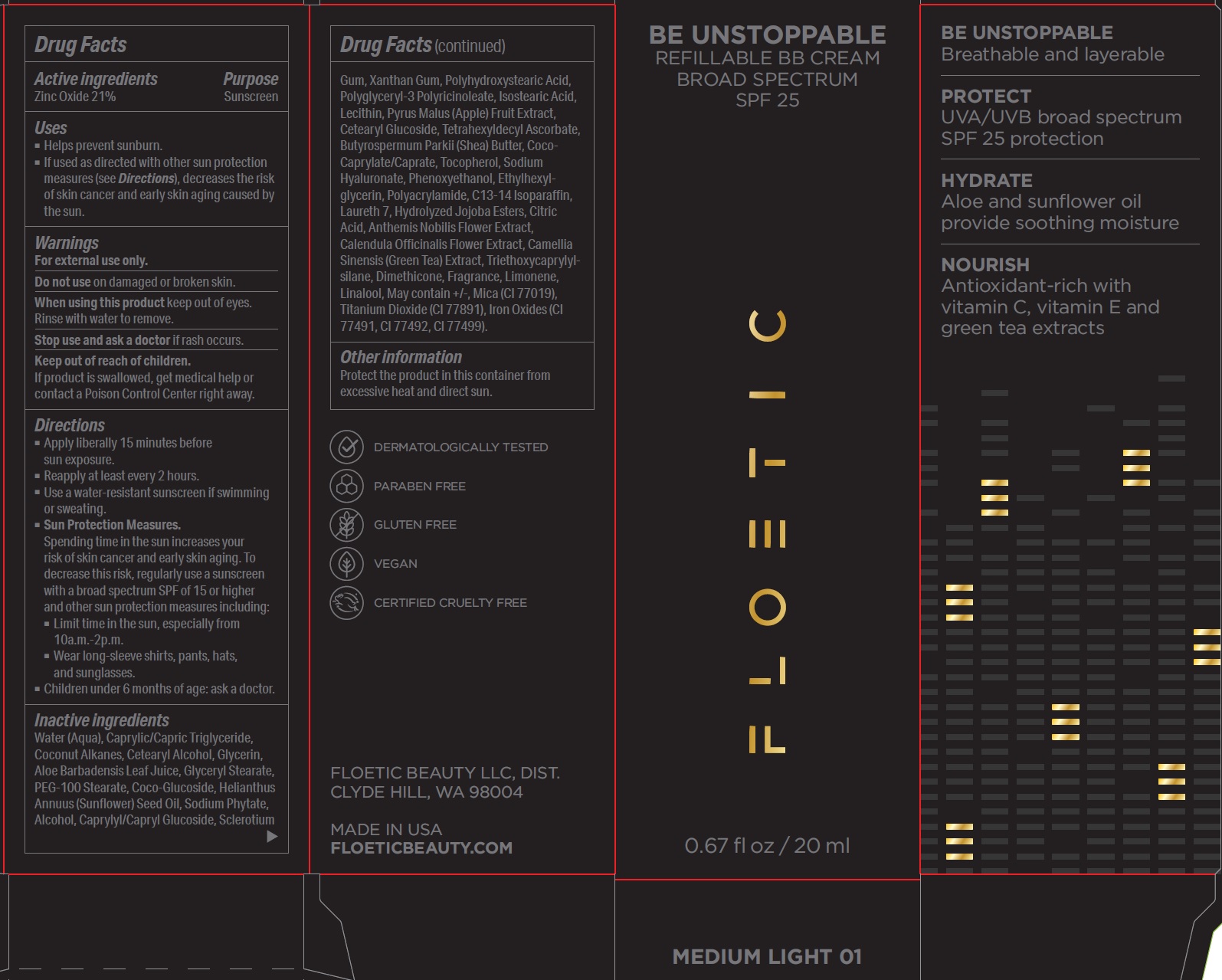 DRUG LABEL: BB Cream Broad Spectrum SPF 25 Medium Light 01
NDC: 62742-4179 | Form: CREAM
Manufacturer: Allure Labs Inc
Category: otc | Type: HUMAN OTC DRUG LABEL
Date: 20191121

ACTIVE INGREDIENTS: ZINC OXIDE 210 mg/1 mL
INACTIVE INGREDIENTS: WATER; MEDIUM-CHAIN TRIGLYCERIDES; COCONUT ALKANES; CETOSTEARYL ALCOHOL; GLYCERIN; ALOE VERA LEAF; GLYCERYL MONOSTEARATE; PEG-100 STEARATE; COCO GLUCOSIDE; SUNFLOWER OIL; PHYTATE SODIUM; ALCOHOL; CAPRYLYL/CAPRYL OLIGOGLUCOSIDE; BETASIZOFIRAN; XANTHAN GUM; POLYHYDROXYSTEARIC ACID (2300 MW); POLYGLYCERYL-3 RICINOLEATE; ISOSTEARIC ACID; LECITHIN, SOYBEAN; APPLE; CETEARYL GLUCOSIDE; TETRAHEXYLDECYL ASCORBATE; SHEA BUTTER; COCO-CAPRYLATE/CAPRATE; TOCOPHEROL; HYALURONATE SODIUM; PHENOXYETHANOL; ETHYLHEXYLGLYCERIN; POLYACRYLAMIDE (10000 MW); C13-14 ISOPARAFFIN; LAURETH-7; HYDROLYZED JOJOBA ESTERS (ACID FORM); CITRIC ACID MONOHYDRATE; CHAMAEMELUM NOBILE FLOWER; CALENDULA OFFICINALIS FLOWER; GREEN TEA LEAF; TRIETHOXYCAPRYLYLSILANE; DIMETHICONE; LIMONENE, (+)-; LINALOOL, (+/-)-; MICA; TITANIUM DIOXIDE; FERRIC OXIDE YELLOW; FERRIC OXIDE RED; FERROSOFERRIC OXIDE

DRUG FACTS

Active Ingredients:

Zinc Oxide 21.0%

Purpose: Sunscreen

Uses:

- Helps prevent sunburn.
- If used as directed with other sun protection measures, decreases the risk of skin cancer and early skin aging caused by the sun.

WARNINGS AND PRECAUTIONS

Warning: For external use only.

Do not use: on damaged or broken skin.

When using this products:

- Keep out of eyes.
- Rinse with water to remove.

Stop use and ask a doctor: If rash occurs.

Keep out of reach of children:

- If product is swallowed, get medical help or contact a Poison Control Center right away.

Directions:

- Apply generously 15 minutes before sun exposer.
- Reapply at least every 2 hours.
- Use a water resistant sunscreen if swimming or sweating. Immediatly after towel drying. at least every 2 hours.
- Sun protection measures.Spending time in the sun increase your risk of skin cancer and early skin aging. To decrease this risk, regularly use a sunscreen with a Broad Spectrum SPF of 15 or higher and other sun protection measures including:
- Limit time in the sun, especially from 10 a.m. - 2 p.m.
- Wear long sleeve shirts, pants, hats and sunglasses.
- Children under 6 months: ask a doctor.

OTHER SAFETY INFORMATION

Protect the product in this container from excessive heat and direct sun.

INACTIVE INGREDIENT

Inactive Ingredients: Water (Aqua), Caprylyc/Capric Triglyceride, Coconut Alkanes, Cetearyl Alcohol, Glycerin, Aloe Barbadensis Leaf Juice, Glyceryl Stearate, PEG-100 Stearate, Coco-Glucoside, Helianthus Annus, Caprylyl/Capryl Glucoside, Sclerotium Gum, Xanthan Gum, Polyglyceryl-3 Polyricinoleate, Isostearic Acid, Lecithin, Pyrus Malus (Apple) Fruit Extract, Cetearyl Glucoside, Tetrahexyldecyl Ascorbate, Butyrospermum Parkii (Shea) Butter, Coco-Caprylate/Caprate, Tocopherol, Sodium Hyaluronate, Phenoxyethanol, Ethylhexylglycerin, Polyacrylamide, C13-14 Isoparaffin, Laureth 7, Hydrolyzed Jojoba Esters, Citric Acid, Anthemis Nobilis Flower Extract, Calendula Officinalis Flower Extract, Camellia Sinensis (Green Tea) Extract, Triethoxycaprylylsilane, Dimethicone, Fragrance, Limonene, Linalool, May contain +/-, Mica (Cl 77019), Titanium Dioxide (Cl 77891), Iron Oxides (Cl77491, Cl77492, Cl 77499).

PACKAGE LABEL

FLOETIC BEAUTY LLC, DIST.

CLYDE HILL, WA 98004

MADE IN USA

WWW.FLOETICBEAUTY.COM